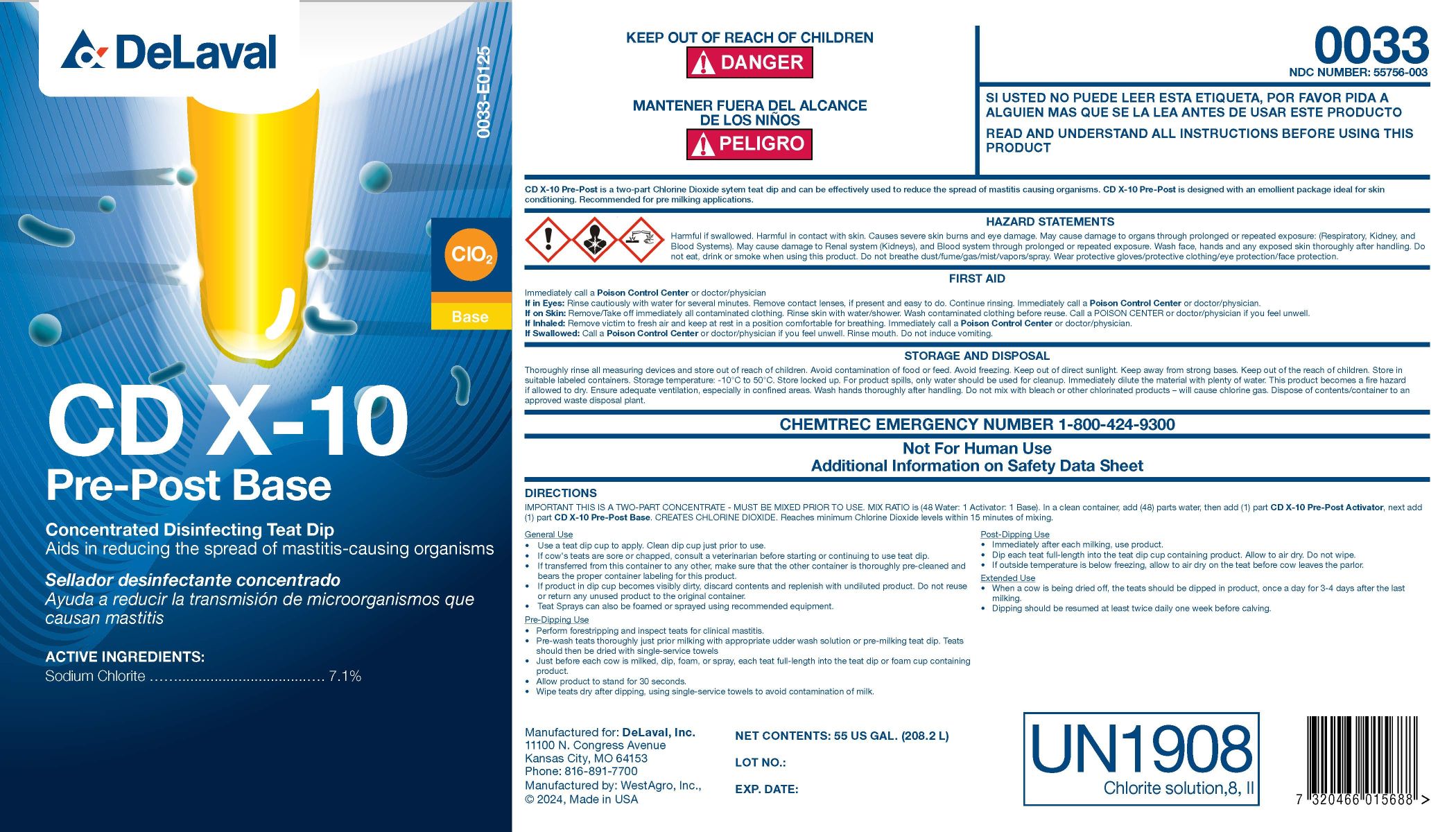 DRUG LABEL: CD X-10 Pre-Post Base
NDC: 55756-003 | Form: CONCENTRATE
Manufacturer: DeLaval
Category: animal | Type: OTC ANIMAL DRUG LABEL
Date: 20250224

ACTIVE INGREDIENTS: SODIUM CHLORITE 71 g/1 L
INACTIVE INGREDIENTS: water

CD X-10 Pre-Post Base

PURPOSE

Concentrated Disinfecting Teat Dip

Aids in reducing the spread of mastitis-causing organisms

ACTIVE INGREDIENTS:

Sodium Chlorite .............................. 7.1%

KEEP OUT OF REACH OF CHILDREN

! DANGER

WARNINGS AND PRECAUTIONS

READ AND UNDERSTAND ALL INSTRUCTIONS BEFORE USING THIS PRODUCT

INDICATIONS AND USAGE

CD X-10 Pre-Post is a two-part Chlorine Dioxide sytem teat dip and can be effectively used to reduce the spread of mastitis causing organisms. CD X-10 Pre-Post is designed with an emollient package ideal for skin conditioning. Recommended for pre milking applications.

WARNINGS

HAZARD STATEMENTS

Harmful if swallowed. Harmful in contact with skin. Causes severe skin burns and eye damage. May cause damage to organs through prolonged or repeated exposure: (Respiratory, Kidney, and Blood Systems). May cause damage to Renal system (Kidneys), and Blood system through prolonged or repeated exposure. Wash face, hands, and any exposed skin thoroughly after handling. Do not eat, drink or smoke when using this product. Do not breathe dust/fume/gas/mist/vapors/spray. Wear protective gloves/protective clothing/eye protection/face protection.

FIRST AID

Immediately call a Poison Control Center or doctor/physician

If in Eyes: Rinse cautiously with water for several minuete. Remove contact lenses, if present and easy to do. Continue rinsing. Immediately call a Poison Control Center or doctor/physician.

If on Skin: Remove/Take off immediately all contaminated clothing. Rinse skin with water/shower. Wash contaminated clothing before reuse. Call a POISON CENTER of doctor/physician if you feel unwell.

If Inhaled: Remove victim to fresh air and keep at rest in a position comfortable for breathing. Immediately call a Poison Control Center or doctor/physician.

If Swallowed: Call a Poison Control Center or doctor/physician if you feel unwell. Rinse mouth. Do not induce vomiting.

STORAGE AND DISPOSAL

Thoroughly rinse all measuring devices and store out of reach of children. Avoid contamination of food or feed. Avoid freezing. Keep out of direct sunlight. Keep away from strong bases. Keep out of the reach of children. Store in suitable labeled containers. Storage temperature: -10° to 50°C. Store locked up. For product spills, only water should be used for cleanup. Immediately dilute the material with plenty of water. This product becomes a fire hazard if allowed to dry. Ensure adequate ventilation, especially in confined areas. Wash hands thoroughly after handling. Do not mix with bleach or other chlorinated products - will cause chlorine gas. Dispose of contents/container to an approved waster disposal plant.

CHEMTREC EMERGENCY NUMBER 1-800-424-9300

WARNINGS

Not for Human Use

Additional Information on Safety Data Sheet

DIRECTIONS

IMPORTANT THIS IS A TWO-PART CONCENTRATE - MUST BE MIXED PRIOR TO USE. MIX RATIO IS (48 Water: 1 Activator: 1 Base). In a clean container, add (48) parts water, then add (1) part CD X-10 Pre-Post Activator, next add (1) part CD X-10 Pre-Post Base. CREATES CHLORINE DIOXIDE. Reaches minimum Chlorine Dioxide levels within 15 minutes of mixing.

General Use

- Use a teat dip cup to apply. Clean dip cup just prior to use.
- If cow's teats are sore or chapped, consult a veterinarian before starting or continuing to use teat dip.
- If transferred from this container to any other, make sure that the other container is thoroughly pre-cleaned and bears the proper container labeling for this product.
- If product in dip cup becomes visibly dirty, discard contents and replenish with undiluted product. Do not reuse or return any unused product to the original container.
- Teat Sprays can also be foamed or sprayed using recommended equipment.

Pre-Dipping Use

- Perform forestripping and inspect teats for clinical mastitis.
- Pre-wash teats thoroughly just prior milking with appropriate udder wash solution or pre-milking teat dip. Teats should then be dried with single-service towels.
- Just before each cow is milked, dip, foam, or spray, each teat full-length into the teat dip or foam cup containing product.
- Allow product to stand for 30 seconds.
- Wipe teats dry after dipping, using single-service towels to avoid contamination of milk.

Post-Dipping Use

- Immediately after each milking, use product.
- Dip each teat full-length into the teat dip cup containing product. Allow to air dry. Do not wipe.
- If outside temperature is below freezing, allow to air dry on the teat before cow leaves the parlor.

Extended Use

- When a cow is being dried off, the teats should be dipped in product, once a day for 3-4 days after the last milking.
- Dipping should be resumed at least twice daily one week before calving.

UN1908

Chlorite solution, 8, ll

NET CONTENTS: US GAL (L)

LOT NO.:

EXP. DATE:

Manufactured for: DeLaval, Inc.

11100 N. Congress Avenue

Kansas City, MO 64153

Phone: 816-891-7700

Manufactured by: WestAgro, Inc.,

© 2024, Made in USA

PACKAGE LABEL

Add image transcription here...